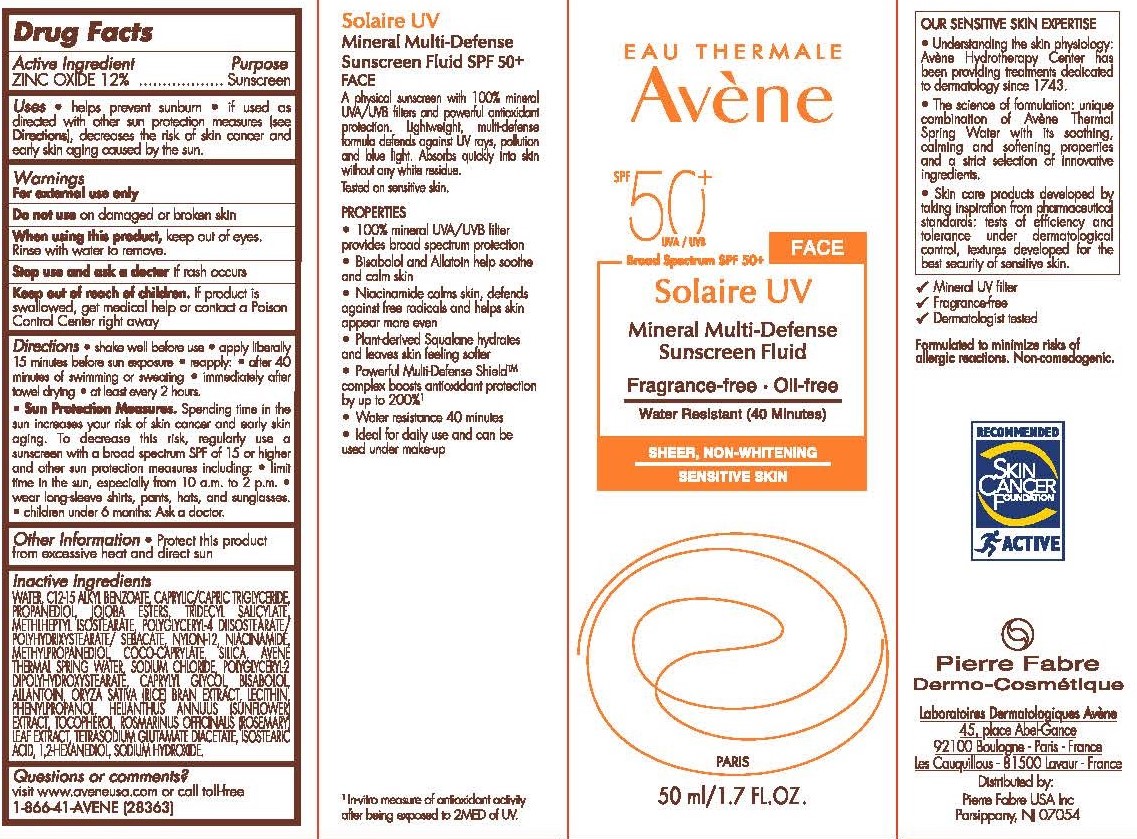 DRUG LABEL: Avene Solaire UV Mineral Sunscreen
NDC: 64760-724 | Form: LOTION
Manufacturer: Pierre Fabre USA Inc.
Category: otc | Type: HUMAN OTC DRUG LABEL
Date: 20240119

ACTIVE INGREDIENTS: ZINC OXIDE 120 mg/1 mL
INACTIVE INGREDIENTS: ROSEMARY OIL; LEVOMENOL; TRIDECYL SALICYLATE; SILICON DIOXIDE; MEDIUM-CHAIN TRIGLYCERIDES; NIACINAMIDE; TETRASODIUM GLUTAMATE DIACETATE; 1,2-HEXANEDIOL; PROPANEDIOL; SODIUM CHLORIDE; POLYGLYCERYL-2 DIPOLYHYDROXYSTEARATE; CAPRYLYL GLYCOL; ISOSTEARIC ACID; SODIUM HYDROXIDE; JOJOBA OIL; METHYLHEPTYL ISOSTEARATE; NYLON-12; METHYLPROPANEDIOL; COCO-CAPRYLATE; WATER; ALKYL (C12-15) BENZOATE; ALLANTOIN; RICE BRAN OIL; LECITHIN, SUNFLOWER; PHENYLPROPANOL; HELIANTHUS ANNUUS WHOLE; TOCOPHEROL

Avene Solaire UV Mineral Sunscreen SPF 50 PLUS

Purpose

Sunscreen

Active Ingredient

Zinc Oxide 12%

Uses

Helps prevent sunburn.

If used as directed with other sun protection measures (see Directions), decreases the risk of skin cancer and early skin aging caused by the sun.

Warnings

For external use only.

Directions

Shake well before use.

Apply liberally 15 minutes before sun exposure.

Reapply.

After 80 minutes of swimming or sweating.

Immediately after towel dry.

At least every 2 hours.

Sun Protection Measures.

Spending time in the sun increases your risk of skin cancer and early skin aging. To decrease this risk of skin cancer and early skin gaining. To decrease this risk, regularly use a sunscreen with a broad spectrum SPF of 15 or higher and other sun protection measures including:

Limit time in the sun, especially from 10 a.m to 2 p.m.

Wear long-sleeve shirts, pants, hats, and sunglasses.

Children under 6 months: Ask a doctor.

Other information

Protect this product from excessive heat and direct sun.

Inactive ingredients

AVÈNE THERMAL SPRING WATER, C12-15 ALKYL BENZOATE,
CAPRYLIC/CAPRIC TRIGLYCERIDE, PROPANEDIOL, JOJOBA ESTERS,
TRIDECYL SALICYLATE, METHYLHEPTYL ISOSTEARATE, POLYGLYCERYL-4
DIISOSTEARATE/POLYHYDROXYSTEARATE/SEBACATE, NYLON-12,
NIACINAMIDE, METHYLPROPANEDIOL, COCO-CAPRYLATE, SILICA,
SODIUM CHLORIDE, POLYGLYCERYL-2 DIPOLYHYDROXYSTEARATE,
CAPRYLYL GLYCOL, BISABOLOL, ALLANTOIN, ORYZA SATIVA (RICE)
BRAN EXTRACT, LECITHIN, PHENYLPROPANOL, HELIANTHUS
ANNUUS (SUNFLOWER) EXTRACT, TOCOPHEROL, ROSMARINUS
OFFICINALIS (ROSEMARY) LEAF EXTRACT, TETRASODIUM
GLUTAMATE DIACETATE, ISOSTEARIC ACID, 1,2-HEXANEDIOL,
SODIUM HYDROXIDE

Questions or comments?

visit www.aveneusa.com or call toll-free 1-866-41-AVENE (28363)

Principal Display Panel - 50 mL Carton

EAU THERMALE

Avene

SPF 50+

Broad Spectrum

Solaire UV

Mineral Multi-Defense

Sunscreen Fluid

Fragrance-Free

Oil-Free

40-Minute Water Resistance

Sheer, Non-Whitening

For Sensitive Skin

50 ml/1.7 FL. OZ.